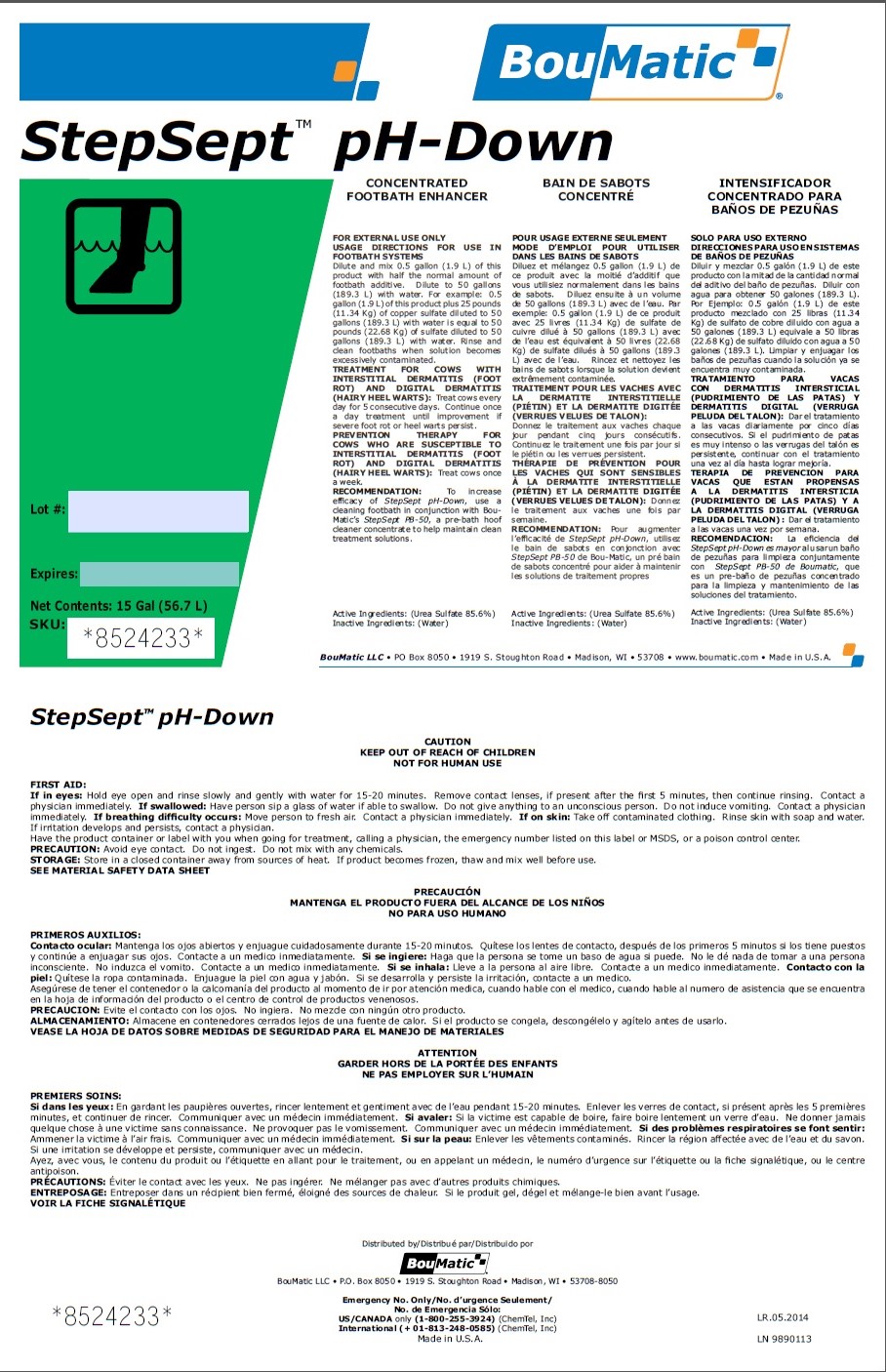 DRUG LABEL: StepSept pH Down
NDC: 48106-1201 | Form: LIQUID
Manufacturer: BouMatic, LLC
Category: animal | Type: OTC ANIMAL DRUG LABEL
Date: 20140601

ACTIVE INGREDIENTS: UREA SULFATE 856 mg/1 L

StepSept pH Down

INDICATIONS AND USAGE

CONCENTRATED FOOTBATH ENHANCER

FOR EXTERNAL USE ONLY

USAGE DIRECTIONS FOR USE IN FOOTBATH SYSTEMS

Dilute and mix 0.5 gallon (1.9 L) of this product with half the normal amount of footbath additive. Dilute to 50 gallons (189.3 L) with water. For example: 0.5 gallon (1.9 L) of this product plus 25 pounds (11.34 Kg) of copper sulfate diluted to 50 gallons (189.3 L) with water is equal to 50 pounds (22.68 Kg) of sulfate diluted to 50 gallons (189.3 L) with water. Rinse and clean footbaths when solution becomes excessively contaminated.

TREATMENT FOR COWS WITH INTERSTITIAL DERMATITIS (FOOT ROT) AND DIGITAL DERMATITIS (HAIRY HEEL WARTS):

Treat cows every day for 5 consecutive days. Continue once a day treatment until improvement if severe foot rot or heel warts persist.

PREVENTION THERAPY FOR COWS WHO ARE SUSCEPTIBLE TO INTERSTITIAL DERMATITIS (FOOT ROT) AND DIGITAL DERMATITIS (HAIRY HEEL WARTS):

Treat cows once a week.

RECOMMENDATION:

To increase efficacy of StepSept pH-Down, use a cleaning footbath in conjunction with Bou-Matic’s StepSept PB-50, a pre-bath hoof cleaner concentrate to help maintain clean treatment solutions.

Active Ingredients: Urea Sulfate 85.6%
Inactive Ingredients: Water

PRECAUTIONS

CAUTION

KEEP OUT OF REACH OF CHILDREN

NOT FOR HUMAN USE

FIRST AID:

If in eyes: Hold eye open and rinse slowly and gently with water for 15-20 minutes. Remove contact lenses, if present after the first 5 minutes, then continue rinsing. Contact a
physician immediately.

If swallowed: Have person sip a glass of water if able to swallow. Do not give anything to an unconscious person. Do not induce vomiting. Contact a physician
immediately.

If breathing difficulty occurs: Move person to fresh air. Contact a physician immediately.

If on skin: Take off contaminated clothing. Rinse skin with soap and water. If irritation develops and persists, contact a physician.

Have the product container or label with you when going for treatment, calling a physician, the emergency number listed on this label or MSDS, or a poison control center.

PRECAUTION: Avoid eye contact. Do not ingest. Do not mix with any chemicals.

STORAGE: Store in a closed container away from sources of heat. If product becomes frozen, thaw and mix well before use.

SEE MATERIAL SAFETY DATA SHEET